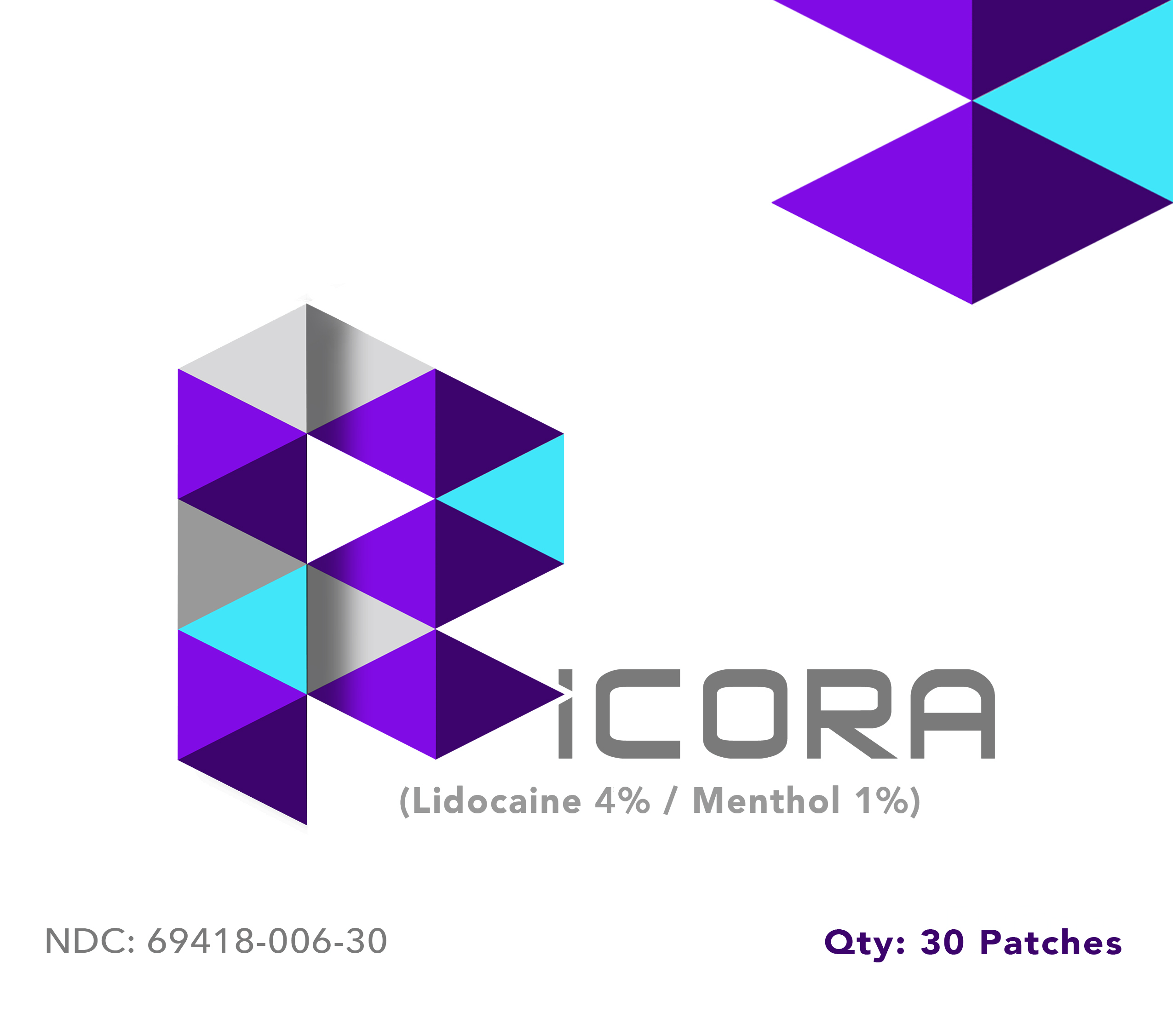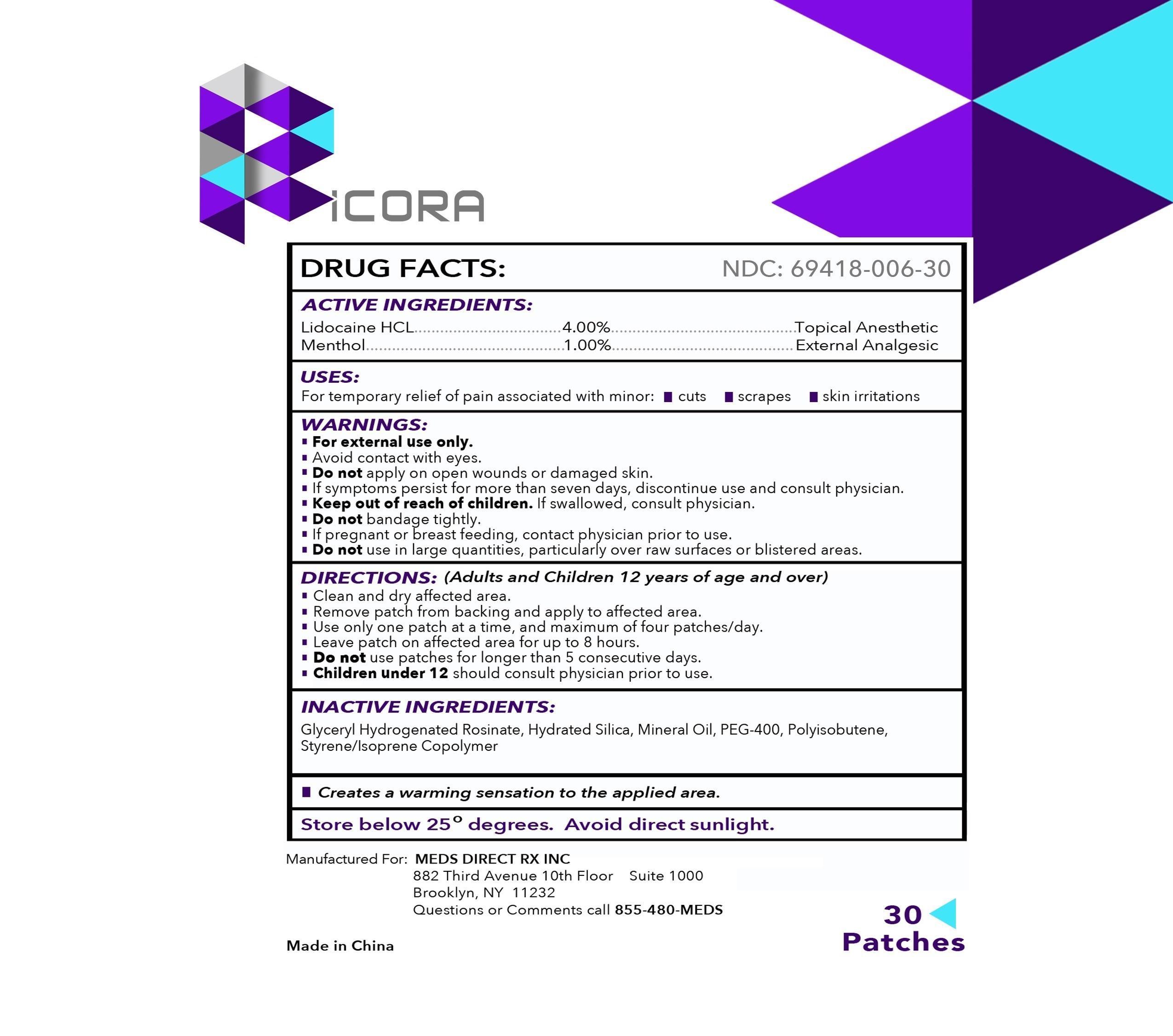 DRUG LABEL: Ricora
NDC: 69418-006 | Form: PATCH
Manufacturer: Meds Direct Rx, Inc.
Category: otc | Type: HUMAN OTC DRUG LABEL
Date: 20151201

ACTIVE INGREDIENTS: LIDOCAINE HYDROCHLORIDE 4 mg/1 g; MENTHOL 1 mg/1 g
INACTIVE INGREDIENTS: HYDRATED SILICA; MINERAL OIL; POLYETHYLENE GLYCOL 400

Ricora Patch

ACTIVE INGREDIENTS:

Lidocaine HCL 4.00%
Menthol 1.00%

PURPOSE

Topical Anesthetic

External Analgesic

USES:

For temporary relief of pain associated with minor: •cuts •scrapes •skin irritations

WARNINGS:

• For external use only.
• Avoid contact with eyes.
• Do not apply on open wounds or damaged skin.
• If symptoms persist for more than seven days, discontinue use and consult physician.

• Keep out of reach of children.

If swallowed, consult physician.

• Do not bandage tightly.

If pregnant or breastfeeding,

contact physician prior to use.

Do not

use in large quantities, particularly over raw surfaces or blistered areas.

DIRECTIONS:

(Adults and Children 12 years of age and over)

• Clean and dry affected area.

• Remove patch from backing and apply to affected area.

• Use only one patch at a time, and maximum of four patches/day.

• Leave patch on affected area for up to 8 hours.

• Do not use patches for longer than 5 consecutive days.

• Children under 12 should consult physician prior to use.

INACTIVE INGREDIENTS:

Glyceryl Hydrogenated Rosinate, Hydrated Silica, Mineral Oil, PEG-400, Polyisobutene, Styrene/Isoprene Copolymer

Creates a warming sensation to the applied area.

Store below 25 degrees. Avoid direct sunlight.